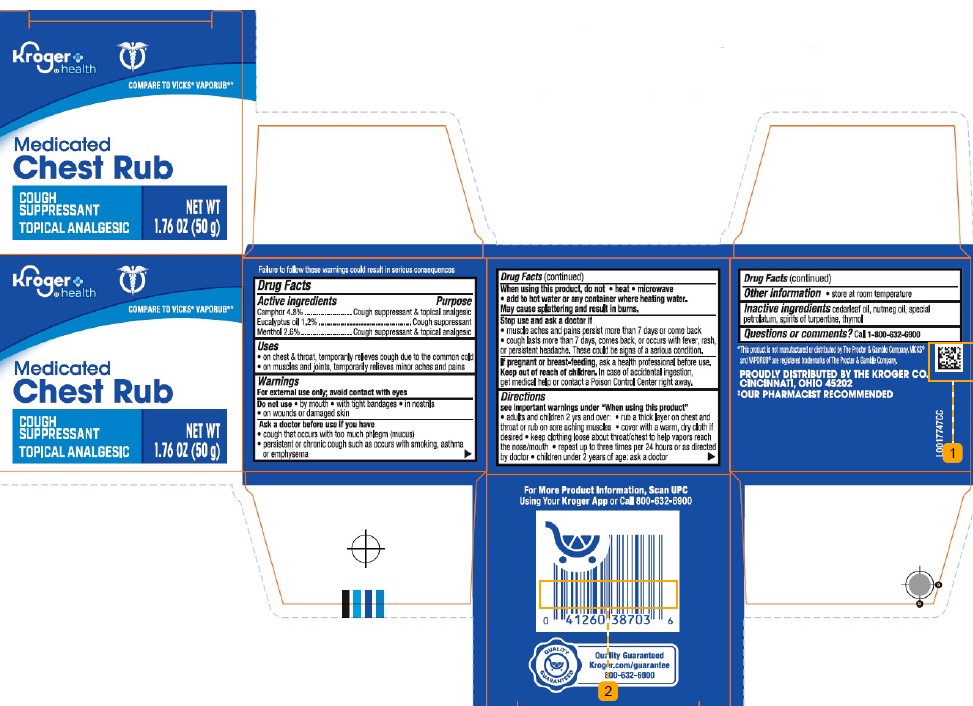 DRUG LABEL: Chest Rub
NDC: 30142-248 | Form: JELLY
Manufacturer: The Kroger Co.
Category: otc | Type: HUMAN OTC DRUG LABEL
Date: 20260227

ACTIVE INGREDIENTS: CAMPHOR (NATURAL) 48 mg/1 g; EUCALYPTUS OIL 12 mg/1 g; MENTHOL 26 mg/1 g
INACTIVE INGREDIENTS: CEDAR LEAF OIL; NUTMEG OIL; PETROLATUM; TURPENTINE OIL; THYMOL

Kroger 248.001/248AI
Medicated Chest Rub

Other safety information

Failure to follow these warnings could result in serious consequences

Active ingredients

Camphor 4.8%

Eucalyptus oil 1.2%

Menthol 2.6%

Purpose

cough suppressant & topical analgesic

Uses

- on chest and throat, temporarily relieves cough due to common cold
- on muscles and joints, temporarily relieves minor aches and pains

Warnings

For external use only; avoid contact with eyes

Do not use

- by mouth
- with tight bandages
- in nostrils
- on wounds or damaged skin

Ask a doctor before use if you have

- cough that occurs with too much phlegm (mucus)
- persistent or chronic cough such occurs with smoking, asthma, or emphysema

When using this product, do not

- heat
- microwave
- add to hot water or any container where heating water.

May cause splattering and result in burns.

Stop use and ask a doctor if

- muscle aches and pains persist more than 7 days or come back
- cough lasts more than 7 days, comes back, or occurs with fever, rash or persistent headache. These could be signs of a serious condition.

If pregnant or breast-feeding,

ask a health professional before use.

Keep out of reach of children.

In case of accidental ingestion, get medical help or contact a Poison Control Center right away.

Directions

See imporatant warning under "When using this product"

- adults & children 2 yrs & over:
- rub a thick layer on chest and throat or rub on sore aching muscles
- cover with warm, dry cloth if desired
- keep clothing loose about throat/chest to help vapors reach the nose/mouth
- repeat up to three times per 24 hours or as directed by doctor
- children under 2 years of age: ask a doctor

Other information

- store at room temperature

Inactive ingredients

cedarleaf oil, nutmeg oil, special petrolatum, spirits of turpentine, thymol

Questions or comments?

Call 1-800-632-6900

Disclaimer

*This product is not manufactured or distributed by The Procter & Gamble Company. VICKS® and VAPORUBare registered trademarks of The Procter & Gamble Company.

ADVERSE REACTION

PROUDLY DISTRIBUTED BY THE KROGER CO.

CINCINNATI, OHIO 45202

‡OUR PHARMACIST RECOMMENED

For More Product Information, Scan UPC Using Your Kroger App or Call 800-632-6900

QUALITY GUARANTEED

Quality Guaranteed

Kroger.com/guarantee

800-632-6900

principal display panel

Kroger®health

COMPARE TO VICKS®VAPORRUB®*

Medicated

Chest Rub

Cough Suppressean

Topical Analgesic

NET WT 1.76 OZ (50 g)